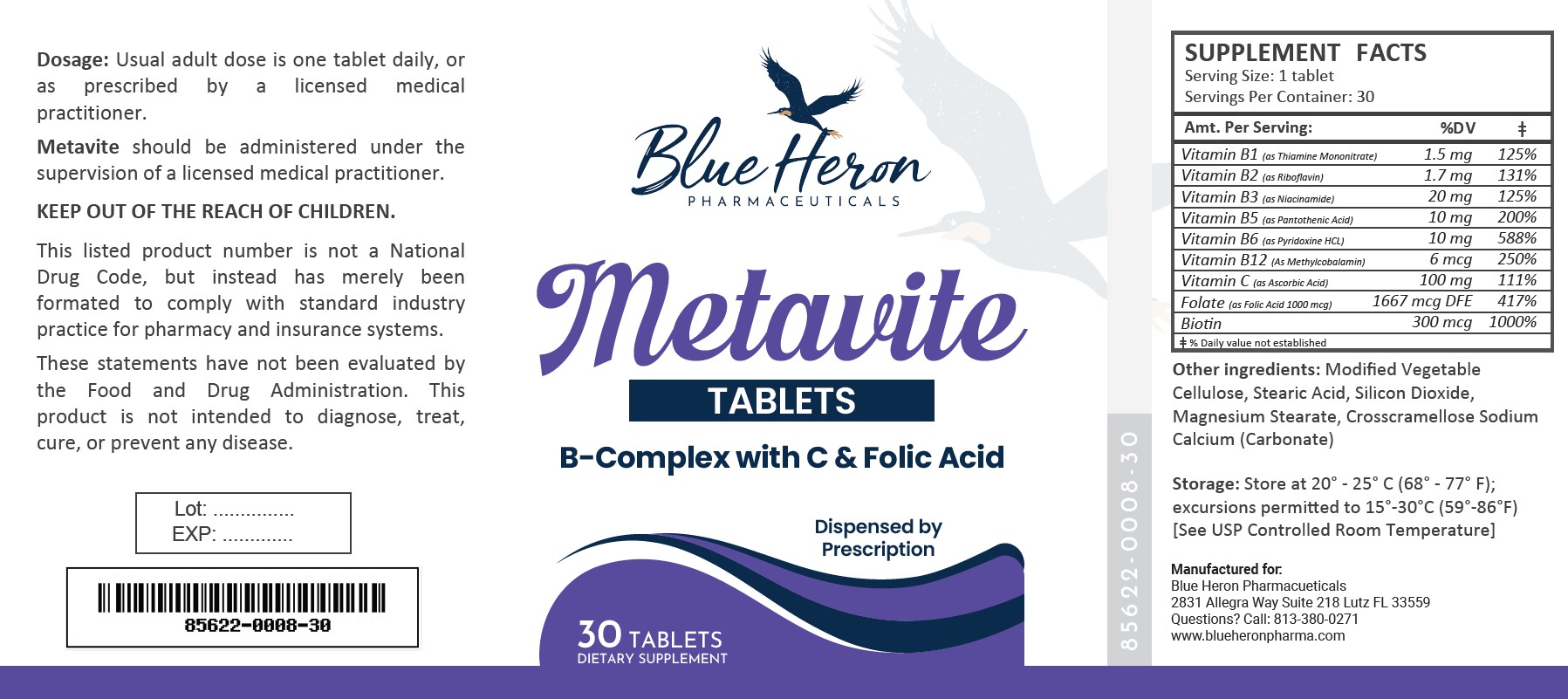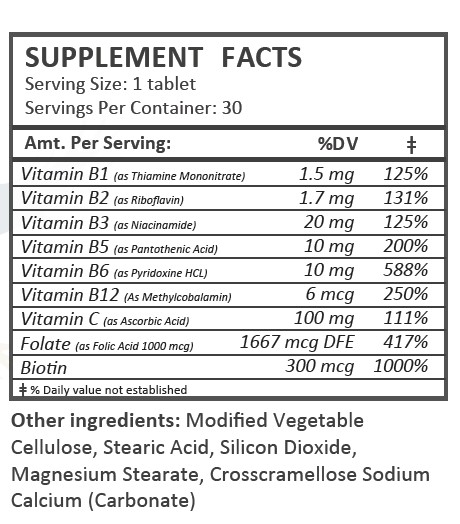 DRUG LABEL: Metavite
NDC: 85622-008 | Form: TABLET
Manufacturer: Blue Heron Pharmaceuticals, LLC
Category: other | Type: DIETARY SUPPLEMENT
Date: 20260129

ACTIVE INGREDIENTS: ASCORBIC ACID 100 mg/1 1; THIAMINE MONONITRATE 1.5 mg/1 1; RIBOFLAVIN 1.7 mg/1 1; NIACINAMIDE 20 mg/1 1; PYRIDOXINE HYDROCHLORIDE 10 mg/1 1; FOLIC ACID 1 mg/1 1; METHYLCOBALAMIN 6 ug/1 1; BIOTIN 300 ug/1 1; PANTOTHENIC ACID 10 mg/1 1

Metavite

Health Claim:

Metavite Tablets

Dispensed by Prescription

Description:

Metavite Multivitamin Tablets are white, round tablets in plastic bottles of 30 ct.

85622-0008-30

Reserved for Professional Recommendation

Metavite Multivitamin Tablets are an orally administered prescription vitamin to provide significant amounts of Vitamins B6, B12, C, riboflavin, niacinamide, thiamine monoitrate, and folate to supplement the diet, and to help assure that nutritional deficiencies of these vitamines will not develop.

Metavite Multivitamin Tablets should be administered under the supervision of a licensed medical practitioner.

This listed product is not a National Drug Code, but instead has merely been formatted to comply with standard industry practice for pharmacy and insurance computer systems.

These statements have not been evaluated by the Food and Drug Administration. This product is not intended to diagnose, treat, cure or prevent any disease.

All prescriptions using this product shall be pursuant to state statutes as applicable. This is not an Orange Book product. This product may be administered only under a physician’s supervision. There are no implied or explicit claims on therapeutic equivalence.

Manufactured for:

Blue Heron Pharmaceuticals

Lutz, FL 33559

Warnings:

This product is contraindicated in patients with a known hypersensitivity to any of the ingredients.

Metavite Multivitamin Tablets should only be used under the direction and supervision of a licensed medical practitioner. Use with caution in patients that may have a medical condition, are pregnant, lactating, trying to conceive, under the age of 18, or taking medications.

These statements have not been evaluated by the Food and Drug Administration. This product is not intended to diagnose, treat, cure, or prevent any disease.

Dosage:

Usual adult dose is 1 tablet by mouth daily once daily, or as prescribed by a licensed medical practitioner.

Precautions:

CONTRAINDICATIONS
This product is contraindicated in patients with known hypersensitivity to any of the ingredients.

PRECAUTIONS
This product is contraindicated in patients with a known hypersensitivity to any of the ingredients.

ADVERSE REACTIONS
Allergic sensitizations have been reported following oral administration of folic acid. Consult your physician immediately if adverse side effects occur.

KEEP OUT OF THE REACH OF CHILDREN.

Storage:

Store at 20° to 25°C (68° to 77°F; excursions permitted to 15° to 30°C (59° to 86°F) [See USP Controlled Room Temperature]